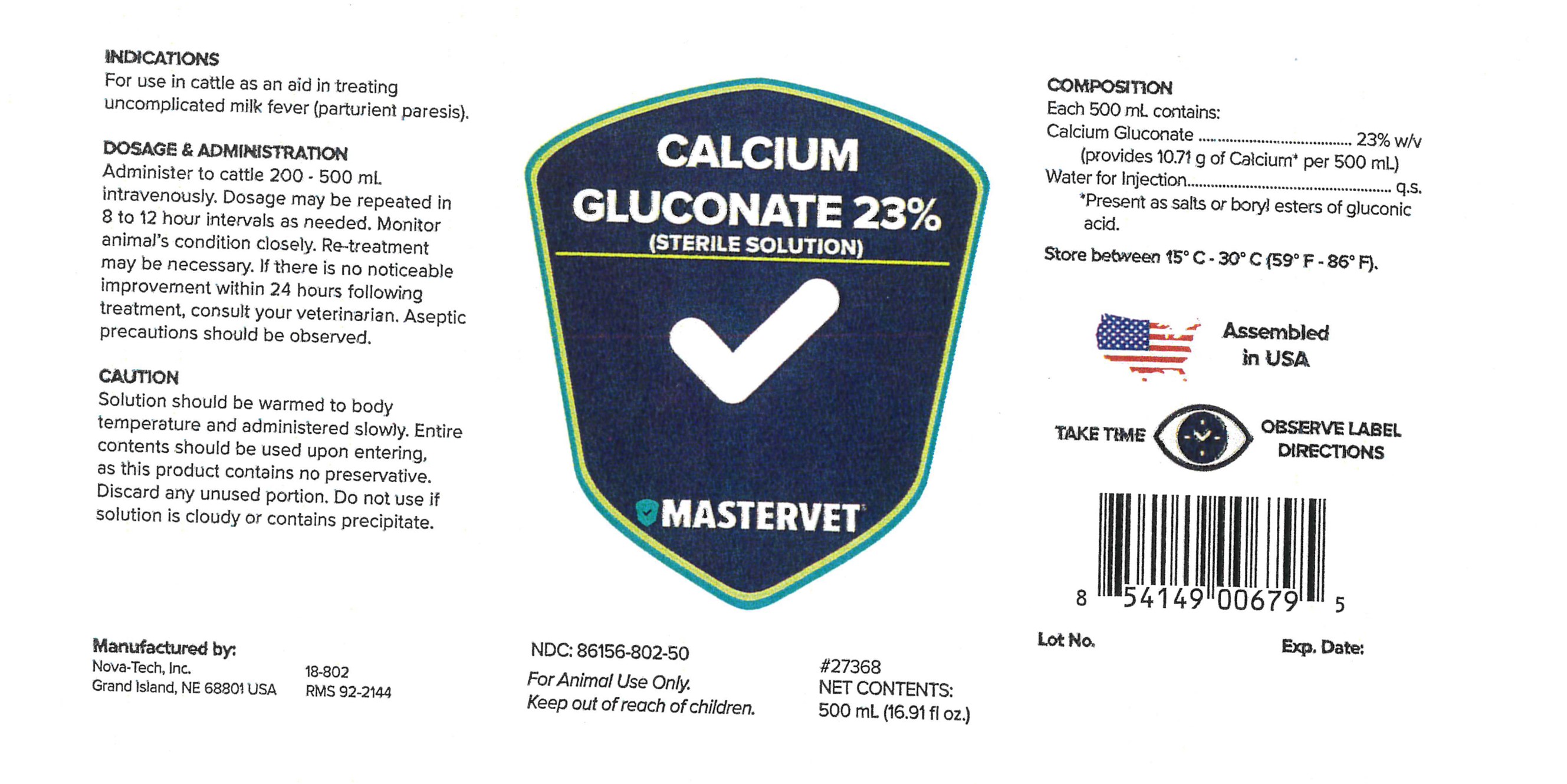 DRUG LABEL: Calcium Gluconate
NDC: 86156-802 | Form: INJECTION, SOLUTION
Manufacturer: MasterVet
Category: animal | Type: OTC ANIMAL DRUG LABEL
Date: 20221227

ACTIVE INGREDIENTS: CALCIUM GLUCONATE 23 g/100 mL

CALCIUM GLUCONATE 23%

INDICATIONS

For use in cattle as an aid in treating uncomplicated milk fever (parturient paresis).

DOSAGE & ADMINISTRATION

Administer to cattle 200 - 500 mL intravenously. Dosage may be repeated in 8 to 12 hour intervals as needed. Monitor animal's condition closely. Re-treatment may be necessary. If there is no noticeable improvement within 24 hours following treatment, consult your veterinarian. Aseptic precautions should be observed.

Caution

Solution should be warmed to body temperature and administered slowly. Entire contents should be used upon entering, as this product contains no preservative. Discard any unused portion. Do not use if solution is cloudy or contains precipitate.

PRECAUTIONS

TAKE TIME OBSERVE LABEL DIRECTIONS

INFORMATION FOR OWNERS/CAREGIVERS

Manufactured by:

Nova-Tech Inc.

Grand Island, NE 68801 USA

18-802

RMS 92-2144

NDC# 86156-802-50

#27368

Net Contents:

500 mL (16.91 fl oz)

Assembled in USA

Lot No.

Exp. Date:

Composition

Each 500 mL Contains:

Calcium Gluconate ..................................... 23% w/v

(provides 10.71 g of Calcium* per 500 mL)

Water for Injection ...................................................... q.s.

*Present as salts or boryl esters of gluconic acid.

STORAGE AND HANDLING

Store between 15°C - 30°C (59°F - 86°F).

GENERAL PRECAUTIONS

FOR ANIMAL USE ONLY.

KEEP OUT OF REACH OF CHILDREN.